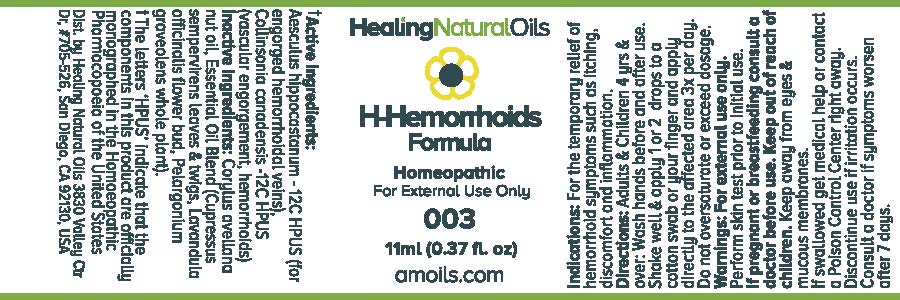 DRUG LABEL: H-Hemorrhoids Formula
                
NDC: 61077-003 | Form: OIL
Manufacturer: Healing Natural Oils
Category: homeopathic | Type: HUMAN OTC DRUG LABEL
Date: 20171211

ACTIVE INGREDIENTS: AESCULUS HIPPOCASTANUM FLOWER 12 [hp_C]/11 mL; COLLINSONIA CANADENSIS ROOT 12 [hp_C]/11 mL
INACTIVE INGREDIENTS: EUROPEAN HAZELNUT OIL; CUPRESSUS SEMPERVIRENS LEAFY TWIG; LAVANDULA ANGUSTIFOLIA FLOWER; PELARGONIUM GRAVEOLENS WHOLE

Active Ingredients:

Aesculus hippocastanum-12C HPUS

Collinsonia canadensis-12C HPUS

Purpose

Aesculus hippocastanum-12C HPUS (for engorged hemorrhoidal veins),

Collinsonia canadensis-12C HPUS (vascular engorgement, hemorrhoids)

The letters ‘HPUS’ indicate that the components in this product are officially
monographed in the Homoeopathic Pharmacopoeia of the United States

Inactive Ingredients:

Corylus avellana nut oil, Essential Oil Blend (Cupressus sempervirens leaves and twigs,

Lavandula officinalis flower bud, Pelargonium graveolens whole plant)

Indications:

For the temporary relief of hemorrhoid symptoms such as itching, discomfort and inflammation.

Directions:

Adults and Children 4 yrs and over: Wash hands before and after use.
Shake well and apply 1 or 2 drops to a cotton swab or your finger and apply directly to the affected area 3x per day.
Do not oversaturate or exceed dosage.

Warnings:

For external use only.

Perform skin test prior to initial use.

PREGNANCY OR BREAST FEEDING

If pregnant or breastfeeding consult a doctor before use.

Keep out of reach of children.

OTHER SAFETY INFORMATION

Keep away from eyes and mucous membranes. If swallowed get medical help
or contact a Poison Control Center right away.

Discontinue use if irritation occurs.

ASK DOCTOR

Consult a doctor if symptoms worsen after 7 days.

DESCRIPTION

Dist. by Healing Natural Oils 3830 Valley Ctr Dr. #705-526, San Diego, CA 92130, USA

PACKAGE LABEL

Healing Natural Oils

H-Hemorrhoids
Formula

Homeopathic

For External Use Only

003

11ml (0.37 fl. oz)
amoils.com